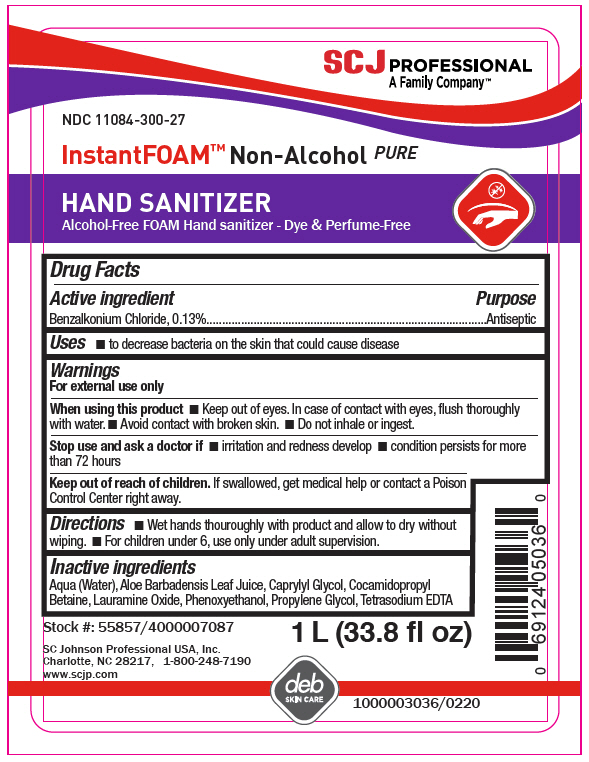 DRUG LABEL: Instant Foam Non-alcohol PURE Hand Sanitizer
NDC: 11084-300 | Form: LIQUID
Manufacturer: SC Johnson Professional USA, Inc.
Category: otc | Type: HUMAN OTC DRUG LABEL
Date: 20241218

ACTIVE INGREDIENTS: BENZALKONIUM CHLORIDE 0.13 g/100 mL
INACTIVE INGREDIENTS: WATER; ALOE VERA LEAF; CAPRYLYL GLYCOL; COCAMIDOPROPYL BETAINE; LAURAMINE OXIDE; PHENOXYETHANOL; PROPYLENE GLYCOL; EDETATE SODIUM

Instant Foam™ Non-alcohol PURE Hand Sanitizer

Drug Facts

Active ingredient

Benzalkonium Chloride, 0.13%

Purpose

Antiseptic

Uses

- to decrease bacteria on the skin that could cause disease

Warnings

For external use only

When using this product

- Keep out of eyes. In case of contact with eyes, flush thoroughly with water.
- Avoid contact with broken skin.
- Do not inhale or ingest.

Stop use and ask a doctor if

- irritation and redness develop
- condition persists for more than 72 hours

Keep out of reach of children. If swallowed, get medical help or contact a Poison Control Center right away.

Directions

- Wet hands thouroughly with product and allow to dry without wiping.
- For children under 6, use only under adult supervision.

Inactive ingredients

Aqua (Water), Aloe Barbadensis Leaf Juice, Caprylyl Glycol, Cocamidopropyl Betaine, Lauramine Oxide, Phenoxyethanol, Propylene Glycol, Tetrasodium EDTA

PRINCIPAL DISPLAY PANEL - 1 L Bottle Label

SCJ PROFESSIONAL
A Family Company™

NDC 11084-300-27

InstantFOAM™ Non-Alcohol PURE

HAND SANITIZER
Alcohol-Free FOAM Hand sanitizer - Dye & Perfume-Free

Stock #: 55857/4000007087

SC Johnson Professional USA, Inc.
Charlotte, NC 28217,
1-800-248-7190
www.scjp.com

1 L (33.8 fl oz)

deb
SKIN CARE

1000003036/0220